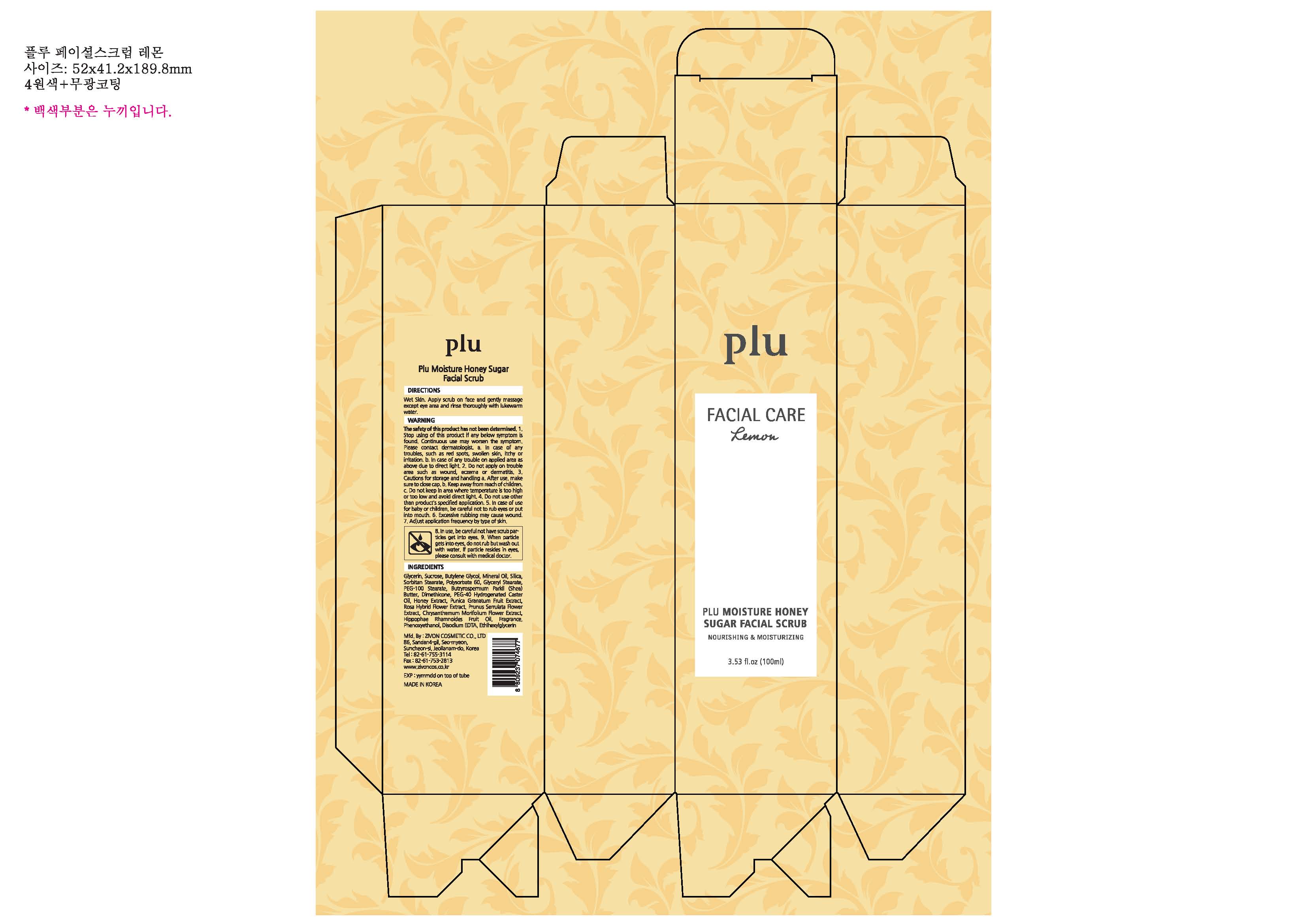 DRUG LABEL: Plu Moisture Honey Sugar Facial Scrub
NDC: 71503-002 | Form: LOTION
Manufacturer: Zivon Cosmetic Co., Ltd.
Category: otc | Type: HUMAN OTC DRUG LABEL
Date: 20170713

ACTIVE INGREDIENTS: Glycerin 49.84 g/100 mL; Dimethicone 1 g/100 mL
INACTIVE INGREDIENTS: Sucrose; Butylene Glycol; Mineral Oil; Polysorbate 60; PEG-100 Stearate; Hippophae Rhamnoides Fruit Oil; Phenoxyethanol

ACTIVE INGREDIENT

Glycerin (49.84%) - Skin Protectant
Dimethicone (1%) - Skin Protectant

INACTIVE INGREDIENT

Sucrose, Butylene Glycol, Mineral Oil, Silica, Sorbitan Stearate, Polysorbate 60, Glyceryl Stearate, PEG-100 Stearate, Butryrospermum Parkii (Shea) Butter, PEG-40 Hydrogenated Caster Oil, Honey Extract, Punica Granatum Fruit Extract, Rosa Hybrid Flower Extract, Prunus Serrulata Flower Extract, Chrysanthemum Morifolium Flower Extract, Hippophae Rhamnoides Fruit Oil, Fragrance, Phenoxyethanol, Disodium EDTA, Ethlhexylglycerin

PURPOSE

Skin Protectant

WARNINGS

The safety of this product has not been determined.
1. Stop using of this product if any below symptom is found. Continuous use may worsen the symptom. Please contact dermatologist. a. In case of any troubles, such as red spots, swollen skin, itchy or irritation. b. In case of any trouble on applied area as above due to direct light.
2. Do not apply on trouble area such as wound, eczema or dermatitis.
3. Cautions for storage and handling a. After use, make sure to close cap. b. Keep away from reach of children. c. Do not keep in area where temperature is too hight or too low and avoid direct light.
4. Do not use other than product's specified application.
5. In case of use for baby or children, be careful not to rub eyes or put into mouth.
6. Excessive rubbing may cause wound.
7. Adjust application frequency by type of skin.
8. In use, be careful not have scrub particles get into eyes.
9. When particle gets into eyes, do not rub but wash out with water. If particle resides in eyes, please consult with medical doctor.

KEEP OUT OF REACH OF CHILDREN

If swallowed, get medical help or contact a Poison Control Center right away

INDICATIONS & USAGE

Wet Skin. Apply scrub on face and gently massage except eye area and rinse thoroughly with lukewarm water.

DOSAGE & ADMINISTRATION

Wet Skin. Apply scrub on face and gently massage except eye area and rinse thoroughly with lukewarm water.